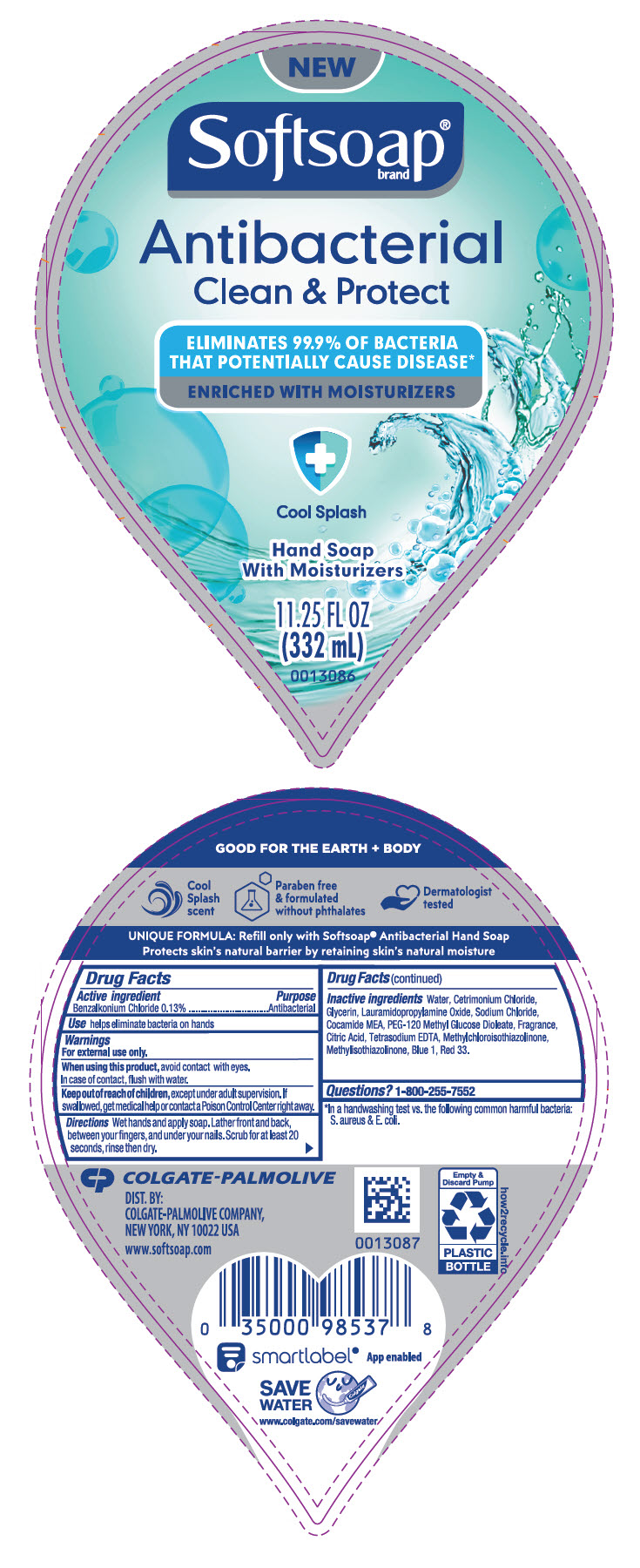 DRUG LABEL: Softsoap Antibacterial Clean and Protect Cool Splash
NDC: 35000-096 | Form: LIQUID
Manufacturer: COLGATE PALMOLIVE COMPANY
Category: otc | Type: HUMAN OTC DRUG LABEL
Date: 20201104

ACTIVE INGREDIENTS: BENZALKONIUM CHLORIDE 1.33 mg/1 mL
INACTIVE INGREDIENTS: WATER; CETRIMONIUM CHLORIDE; GLYCERIN; LAURAMIDOPROPYLAMINE OXIDE; SODIUM CHLORIDE; COCO MONOETHANOLAMIDE; PEG-120 METHYL GLUCOSE DIOLEATE; CITRIC ACID MONOHYDRATE; EDETATE SODIUM; METHYLCHLOROISOTHIAZOLINONE; METHYLISOTHIAZOLINONE; FD&C BLUE NO. 1; D&C RED NO. 33

Softsoap® Antibacterial Clean and Protect Cool Splash

Drug Facts

Active ingredient

Benzalkonium Chloride 0.13%

Purpose

Antibacterial

Use

helps eliminate bacteria on hands

Warnings

For external use only.

When using this product, avoid contact with eyes.

In case of contact, flush with water.

Keep out of reach of children, except under adult supervision. If swallowed, get medical help or contact a Poison Control Center right away.

Directions

Wet hands and apply soap. Lather front and back, between your fingers, and under your nails. Scrub for at least 20 seconds, rinse then dry.

Inactive ingredients

Water, Cetrimonium Chloride, Glycerin, Lauramidopropylamine Oxide, Sodium Chloride, Cocamide MEA, PEG-120 Methyl Glucose Dioleate, Fragrance, Citric Acid, Tetrasodium EDTA, Methylchloroisothiazolinone, Methylisothiazolinone, Blue 1, Red 33.

Questions?

1-800-255-7552

DIST. BY:
COLGATE-PALMOLIVE COMPANY,
NEW YORK, NY 10022 USA

PRINCIPAL DISPLAY PANEL - 332 mL Bottle Label

NEW

Softsoap®
brand

Antibacterial
Clean & Protect

ELIMINATES 99.9% OF BACTERIA
THAT POTENTIALLY CAUSE DISEASE*

ENRICHED WITH MOISTURIZERS

Cool Splash

Hand Soap
With Moisturizers

11.25 FL OZ
(332 mL)

0013086